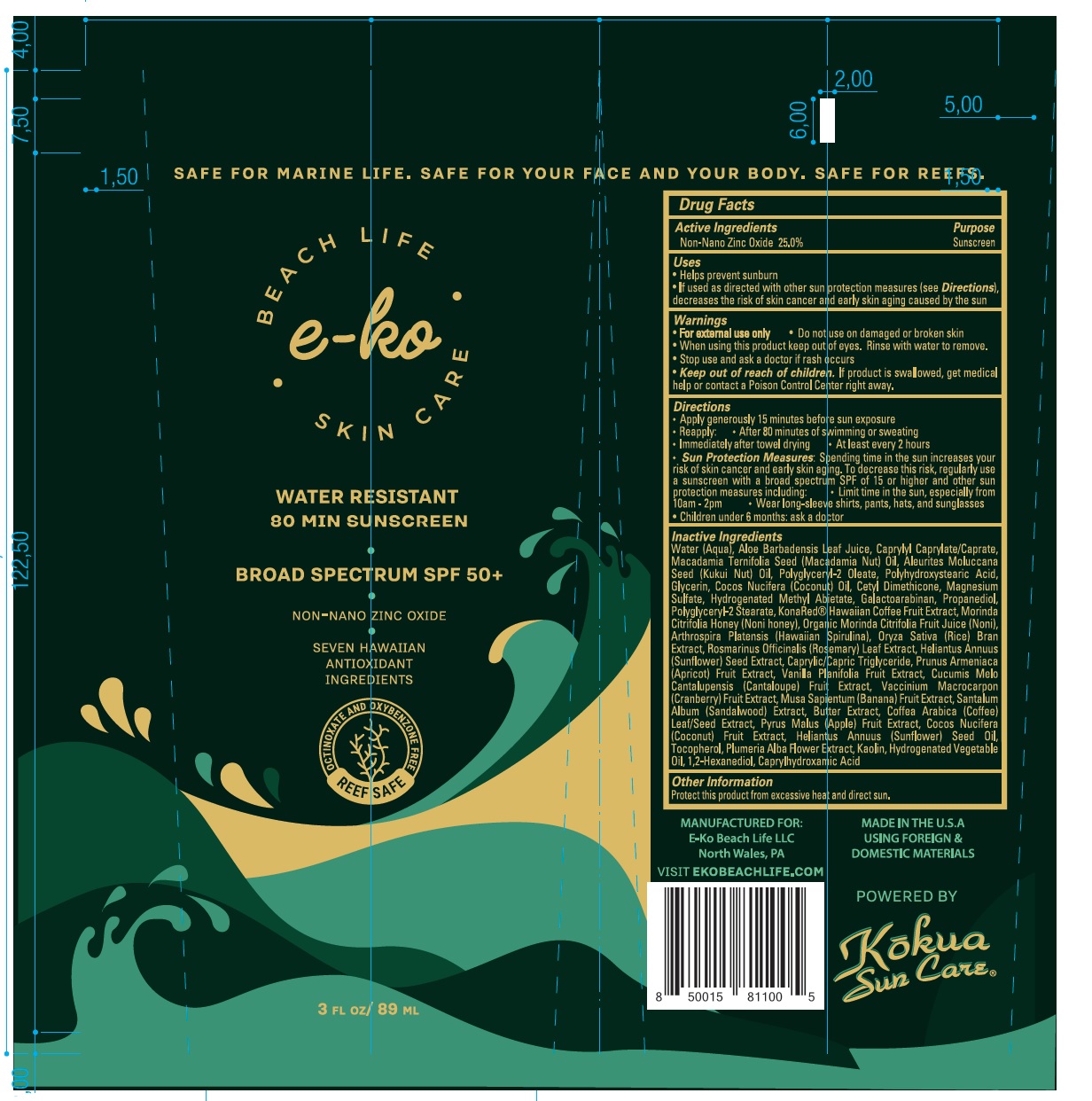 DRUG LABEL: e-ko SKIN CARE
NDC: 73618-001 | Form: LOTION
Manufacturer: E-Ko Beach Life Limited
Category: otc | Type: HUMAN OTC DRUG LABEL
Date: 20220405

ACTIVE INGREDIENTS: ZINC OXIDE 25 g/100 mL
INACTIVE INGREDIENTS: WATER; ALOE VERA LEAF; CAPRYLYL CAPRYLATE/CAPRATE; MACADAMIA OIL; KUKUI NUT OIL; POLYGLYCERYL-2 OLEATE; POLYHYDROXYSTEARIC ACID (2300 MW); GLYCERIN; COCONUT OIL; CETYL DIMETHICONE 25; MAGNESIUM SULFATE, UNSPECIFIED FORM; HYDROGENATED METHYL ABIETATE; GALACTOARABINAN; PROPANEDIOL; POLYGLYCERYL-2 STEARATE; COFFEA ARABICA FRUIT; NONI FRUIT JUICE; ARTHROSPIRA PLATENSIS; RICE BRAN; ROSEMARY; SUNFLOWER SEED; MEDIUM-CHAIN TRIGLYCERIDES; APRICOT; VANILLA BEAN; MUSKMELON; CRANBERRY; BANANA; SANDALWOOD; ARABICA COFFEE BEAN; APPLE; COCONUT; SUNFLOWER OIL; TOCOPHEROL; PLUMERIA ALBA FLOWER; KAOLIN; 1,2-HEXANEDIOL; CAPRYLHYDROXAMIC ACID

e-ko SKIN CARE SPF 50

Active Ingredients

Non-Nano Zinc Oxide 25.0%

Purpose

Sunscreen

Uses

• Helps prevent sunburn
• If used as directed with other sun protection measures (see Directions), decreases the risk of skin cancer and early skin aging caused by the sun

Warnings

• For external use only • Do not use on damaged or broken skin
• When using this product keep out of eyes. Rinse with water to remove.
• Stop use and ask a doctor if rash occurs

Keep out of reach of children. If product is swallowed, get medical help or contact a Poison Control Center right away.

Directions

• Apply generously 15 minutes before sun exposure

• Reapply: • After 80 minutes of swimming or sweating

• Immediately after towel drying • At least every 2 hours

• Sun Protection Measures: Spending time in the sun increases your risk of skin cancer and early skin aging. To decrease this risk, regularly use a sunscreen with a broad spectrum SPF of 15 or higher and other sun protection measures including: • Limit time in the sun, especially from 10am - 2pm • Wear long-sleeve shirts, pants, hats, and sunglasses

• Children under 6 months: ask a doctor

Inactive Ingredients

Water (Aqua), Aloe Barbadensis Leaf Juice, Caprylyl Caprylate/Caprate, Macadamia Ternifolia Seed (Macadamia Nut) Oil, Aleurites Moluccana Seed (Kuki Nut) Oil, Polyglyceryl-2 Oleate, Polyhydroxystearic Acid, Glycerin, Cocos Nucifera (Coconut) Oil, Cetyl Dimethicone, Magnesium Sulfate, Hydrogenated Methyl Abietate, Galactoarabinan, Propanediol, Polyglyceryl-2 Stearate, KonaRed® Hawaiian Coffee Fruit Extract, Morinda Citrifolia Honey (Noni honey), Organic Morinda Citrifolia Fruit Juice (Noni), Arthrospira Platensis (Hawaiian Spirulina), Oryza Sativa (Rice) Bran Extract, Rosmarinus Officinalis (Rosemary) Leaf Extract, Helianthus Annuus (Sunflower) Seed Extract, Caprylic/Capric Triglyceride, Prunus Armeniaca (Apricot) Fruit Extract, Vanilla Planifolia Fruit Extract, Cucumis Melo Cantalupensis (Cantaloupe) Fruit Extract, Vaccinium Macrocarpon (Cranberry) Fruit Extract, Musa Sapientum (Banana) Fruit Extract, Santalum Album (Sandalwood) Extract, Butter Extract, Coffea Arabica (Coffee) Leaf/ Seed Extract, Pyrus Malus (Apple) Fruit Extract, Cocos Nucifera (Coconut) Fruit Extract, Helianthus Annuus (Sunflower) Seed Oil, Tocopherol, Plumeria Alba Flower Extract, Kaolin, Hydrogenated Vegetable Oil, 1,2-Hexanediol, Caprylhydroxamic Acid.

Other Information

Protect this product from excessive heat and direct sun.

SAFE FOR MARINE LIFE. SAFE FOR YOUR FACE AND YOUR BODY. SAFE FOR REEFS

WATER RESISTANT

80 MIN SUNSCREEN

BROAD SPECTRUM SPF 50+

NON- NANO ZINC OXIDE

SEVEN HAWAIIN ANTIOXIDANT INGREDIENTS

OCTINOXATE AND OXYBENZONE FREE

MANUFACTURED FOR

E-Ko Beach Life LLC

North Wales, PA

VISIT EKOBEACHLIFE.COM

MADE IN THE U.S.A

USING FOREIGN & DOMESTIC MATERIALS

POWERED BY Kokua Sun Care®